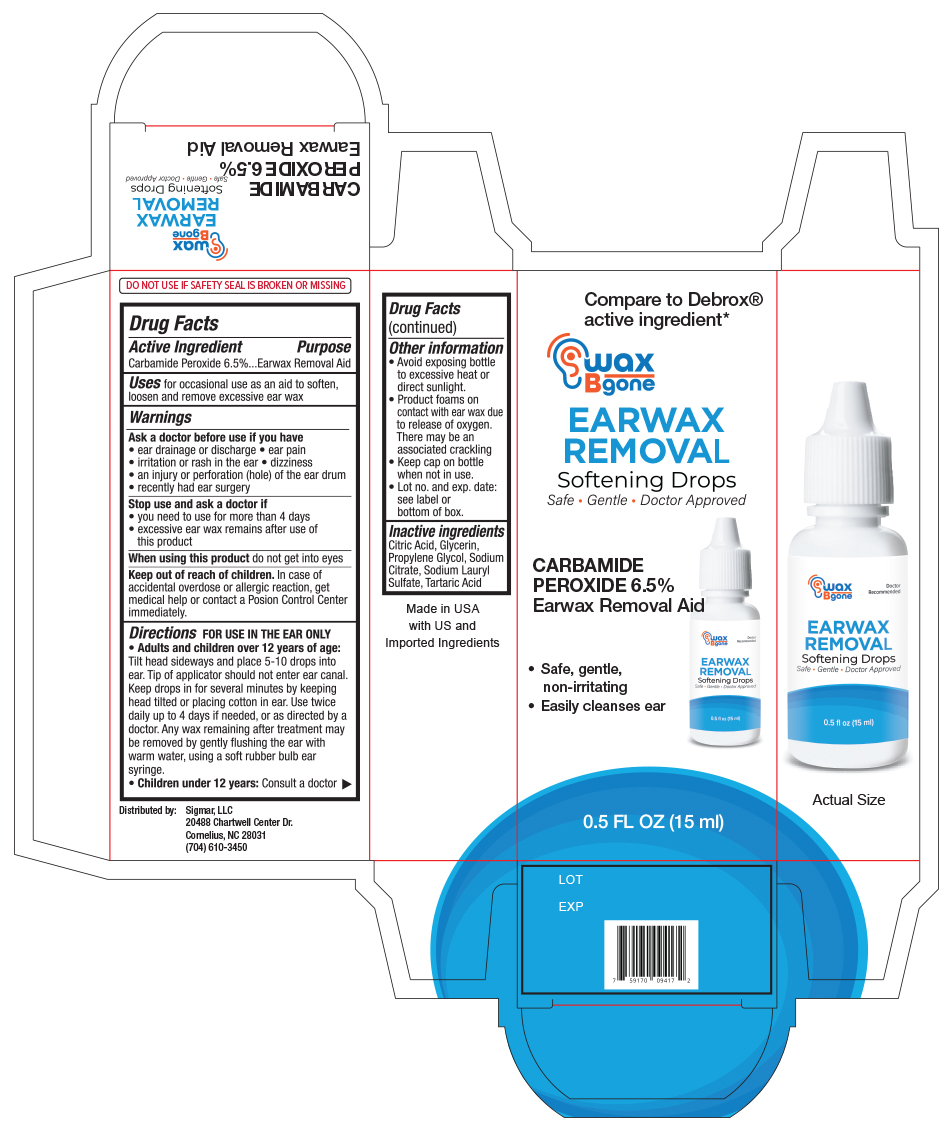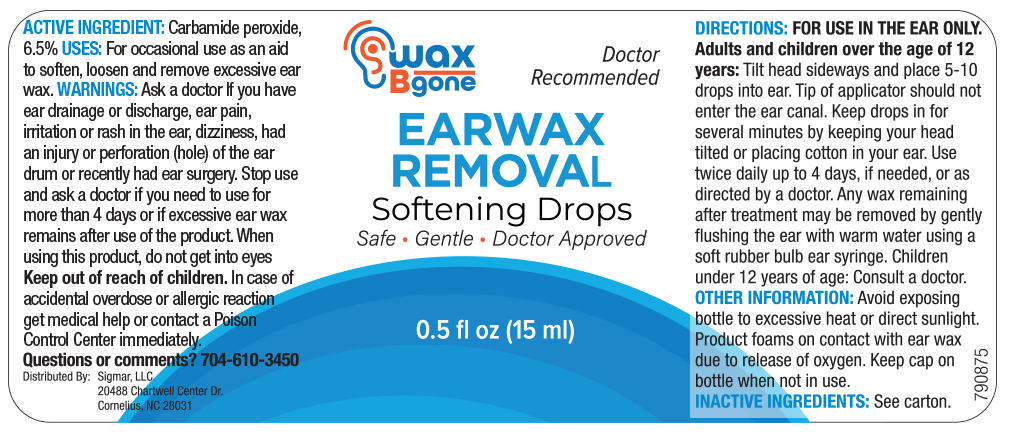 DRUG LABEL: Wax B Gone Ear Wax Removal Drops
NDC: 82498-149 | Form: SOLUTION/ DROPS
Manufacturer: SIGMAR, LLC
Category: otc | Type: HUMAN OTC DRUG LABEL
Date: 20240108

ACTIVE INGREDIENTS: CARBAMIDE PEROXIDE 65 mg/1 mL
INACTIVE INGREDIENTS: GLYCERIN; ANHYDROUS CITRIC ACID; PROPYLENE GLYCOL; SODIUM CITRATE; SODIUM LAURYL SULFATE; TARTARIC ACID

Drug Facts

Active ingredient

Carbamide Peroxide, 6.5%

Purpose

Earwax Removal Aid

Uses

For occasional use as an aid to soften, loosen and remove excessive ear wax.

Warnings

Ask a Doctor before use if you have

- eardrainage, discharge,
- ear pain
- irritation or rash in the ear
- dizziness
- injury or perforation (hole) of the ear drum
- recently had ear surgery

Stop Use and ask a Doctor if

- you need to use for more than 4 days
- execessive ear wax remain after use of this product

When using this product

- do not use for more than four days
- avoid contact with the eyes. If accidental contact with the eyes occurs, flush eyes with water and consult a doctor
- if excessive earwax remains after the use of this product, consult a doctor

Keep out of the reach of children

If swallowed, get medical help or contact a Poison Control Center right away.

Directions FOR USE IN THE EAR ONLY

- Adults and children over 12 years of age:
- Tilt head sideways and place 5 to 10 drops into ear.
- Tip of applicator should not enter ear canal.
- Keep drops in ear for several minutes by keeping head tilted or placing cotton in the ear.
- Use twice daily for up to 4 days if needed, or as directed by a doctor.
- Any earwax remaining after treatment may be removed by gently flushing the ear with warm water, using a soft rubber bulb ear syringe.
- When the ear canal is irrigated, the tip of the ear syringe should not obstruct the flow of water leaving the ear canal.
- Children under 12 years: consult a doctor.

Other information

- Protect from heat and direct sunlight
- product foams on contact with ear wax due ot releae of oxygen, there may be associated cracking
- Keep cap on bottle when not in use.
- Lot No. and EXP date: see label, bottom container or box.

Inactive ingredients

Citric Acid, Glycerin, Propylene Glycol, Sodium Citrate, Sodium Lauryl Sulfate, Tartaric Acid

Principal Display Panel Bottle Label 0.5 FL OZ

Wax B Gone NDC 82498-149-15

Ear Wax Removal drops

Carbamide Peroxide 6.5%

0.5 FL OZ (15ml)

Principal Display Panel - Carton label 0.5 FL OZ

Wax B Gone NDC 82498-149-15

Ear wax Remover Drops

Carbamide Peroxide 6.5%

Ear wax removal aid

0.5 FL OZ (15ml)